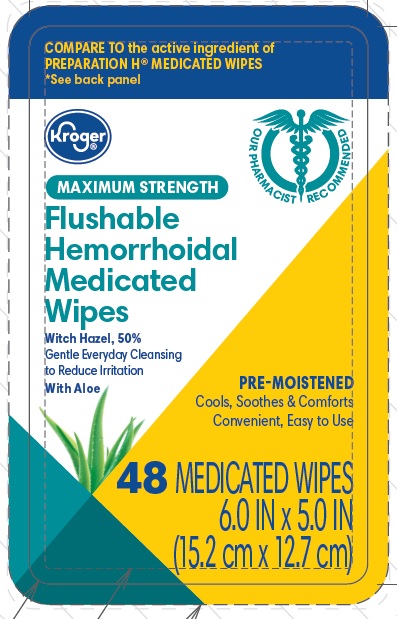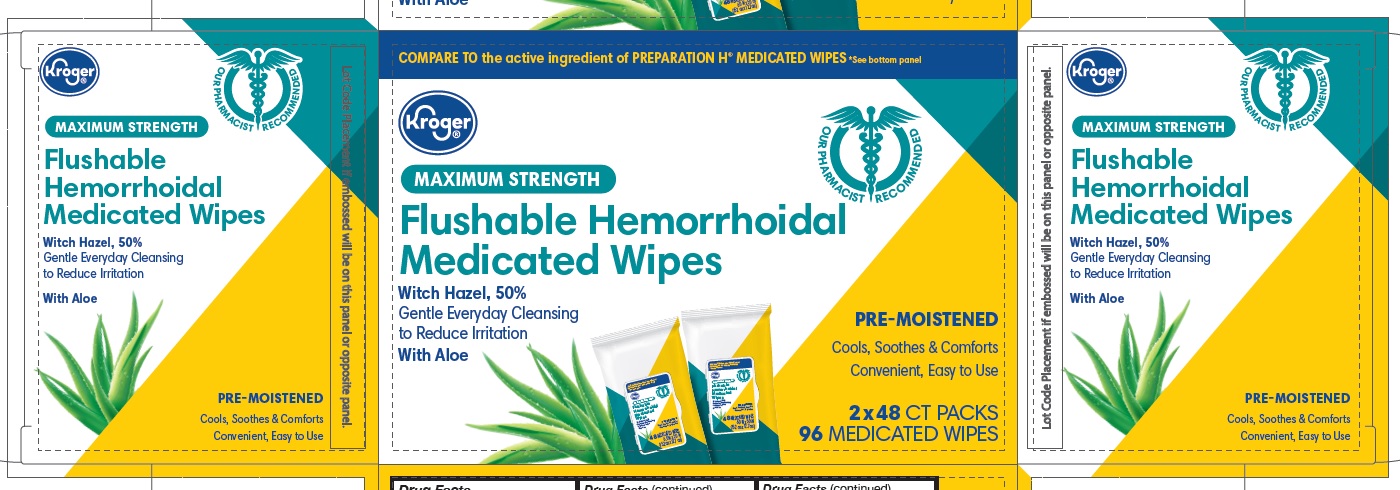 DRUG LABEL: Flushable Hemorrhoidal Medical Wipes
NDC: 30142-314 | Form: PATCH
Manufacturer: Kroger Company
Category: otc | Type: HUMAN OTC DRUG LABEL
Date: 20200331

ACTIVE INGREDIENTS: WITCH HAZEL 500 mg/1000 mg
INACTIVE INGREDIENTS: WATER; ALOE VERA LEAF; SODIUM CITRATE; CITRIC ACID MONOHYDRATE; GLYCERIN; PHENOXYETHANOL; POTASSIUM SORBATE

Drug Facts

Active Ingredient

Witch Hazel 50%

Purpose

Hemorrhoidal Astringent

Uses

Temporarily relieves these external symptoms associated with hemorrhoids:

- itching
- burning
- irritation

Warnings

For external use only.

When using this product

- do not exceed the recommended daily dosage unless directed by a doctor.
- do not insert into rectum or vagina using fingers or mechanical device.

Stop use and ask a doctor if

- rectal bleeding occurs
- condition worsens or does not improve within 7 days.

Keep out of reach of children.

If swallowed, get medical help or contact a Poison Control Center right away at 1-800-222-1222.

Directions

As hemorrhoidal treatment for adults:

- when practical, cleanse the affected area with mild soap and warm water and rinse thoroughly.
- gently dry by patting or blotting with toilet tissue or soft cloth before applying.
- gently apply to the affected area by patting and then discard.
- can be used up to six times daily or after each bowel movement.

Children under 12 years of age

- consult a doctor.

Other Information

Store at controlled room temperature: 15º-30ºC (59º-86ºF)

Inactive Ingredients

Water, Aloe Barbadensis Leaf Extract, Sodium Citrate, Citric Acid, Glycerin, Phenoxyethanol, Potassium Sorbate

OTHER SAFETY INFORMATION

Flush only one wipe at a time. Keep lid tightly closed when not in use.

Gently pull out wipe to dispense

Safe for well-maintained sewers and septic systems

Not recommended for use with basement pump systems

Principal Display Panel

NDC 30142-314-48

COMPARE TO the active ingredient of PREPARATION H® MEDICATED WIPES

*See back panel

Kroger®

MAXIMUM STRENGTH

Flushable Hemorrhoidal Medicated Wipes

Witch Hazel, 50%

Gentle Everyday Cleansing to Reduce Irritation

With Aloe

PRE˜MOISTENED Cools, Soothes & Comforts Convenient, Easy to Use

48 MEDICATED WIPES 6.0 IN x 5.0 IN (15.2 cm x 12.7 cm)

NDC 30142-314-96

COMPARE TO the active ingredient of PREPARATION H® MEDICATED WIPES

*See bottom panel

Kroger®

MAXIMUM STRENGTH

Flushable Hemorrhoidal Medicated Wipes

Witch Hazel, 50%

Gentle Everyday Cleansing to Reduce Irritation

With Aloe

PRE˜MOISTENED Cools, Soothes & Comforts Convenient, Easy to Use

2 X 48 CT PACKS

96 MEDICATED WIPES